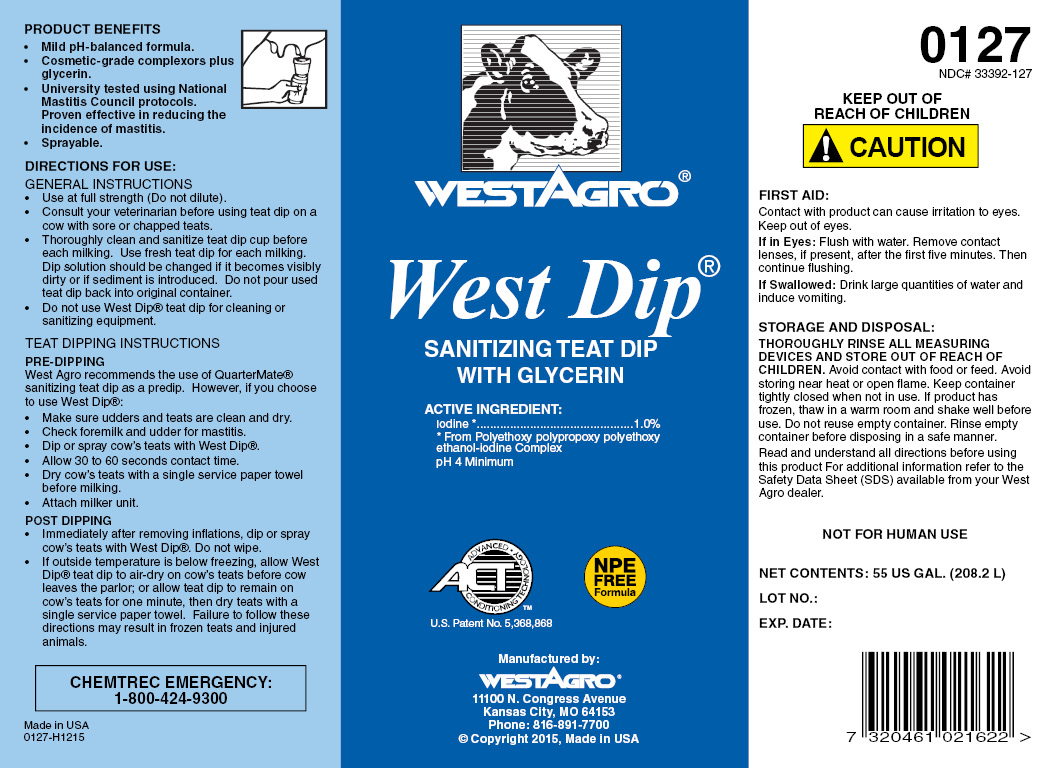 DRUG LABEL: West Dip
NDC: 33392-127 | Form: SOLUTION
Manufacturer: WestAgro, Inc.
Category: animal | Type: OTC ANIMAL DRUG LABEL
Date: 20211213

ACTIVE INGREDIENTS: IODINE 10.2 g/1 L

WESTAGRO West Dip

SANITIZING TEAT DIP

with GLYCERIN

ACTIVE INGREDIENT:
Iodine .................................. 1.0%
From Polyethoxy polypropoxy polyethoxy ethanol-iodine complex
pH 4 Minimum

ACT
ADVANCED CONDITIONIN TECHNOLOGY

U.S. Patent No.
5,368,868

NPE FREE Formula

Manufactured by:
WESTAGRO
11100 N. Congress Ave. Kansas City, MO
64153-1296

PRODUCT BENEFITS

- Mild pH-balanced formula.
- Cosmetic-grade complexors plus glycerin.
- University tested using National Mastitis Council protocols. Proven effective in reducing the incidence of mastitis.
- Sprayable

INDICATIONS AND USAGE

DIRECTIONS FOR USE:
GENERAL INSTRUCTIONS

- Use at full strength (Do not dilute).
- Consult your veterinarian before using teat dip on a cow with sore or chapped teats.
- Thoroughly clean and sanitize teat dip cup before each milking. Dip solution should be changed if it becomes visibly dirty, or if sediment is introduced. Do not pour used teat dip back into original container.
- Do not use West Dip teat dip for cleaning or sanitizing equipment.

TEAT DIPPING INSTRUCTIONS
PRE-DIPPING

West Agro recommends the use of Quarter Mate sanitizing teat dip as a predip. However, if you choose to use West Dip:

- Make sure udder and teats are clean and dry.
- Check foremilk and udder for mastitis.
- Dip or spray cow's teats with West Dip.
- Allow 30 to 60 seconds contact time.
- Dry cow's teats with a single service paper towel before milking.
- Attach milker unit.

POST-DIPPING

- Immediately after removing inflations, dip or spray cow's teats with West Dip. Do not wipe.
- If outside temperature is below freezing, allow West dip teat dip to air-dry on cow's teats before cow leaves the parlor; or allow teat dip to remain on cow's teats for one minute, then dry teats with a single service paper towel. Failure to follow these directions may result in frozen teats and injured animals.

Made in U.S.A.
0127-E0404
Copyright 2004, West Agro, Inc.

0127
NDC 33392-127

KEEP OUT OF REACH OF CHILDREN

! CAUTION

FIRST AID

Contact with product can cause irritation to eyes. Keep out of eyes.

Eye Contact: Flush with water. Remove contact lenses, if present, after the first five minutes. Then continue flushing.

If Swallowed: Drink large quantities of water and induce vomiting.

STORAGE AND DISPOSAL:

THOROUGHLY RINSE ALL MEASURING DEVICES AND STORE OUT OF REACH OF CHILDREN. Avoid contact with food or feed. Avoid storing near heat or open flame. Keep container tightly closed when not in use. If product has frozen, thaw in a warm room and shake well before use. Do not reuse empty container. Rinse empty container before disposing in a safe manner.

Read and understand all directions before using this product. For additional information refer to the Material Safety Data Sheet (MSDS) available from your West Agro dealer.

CHEMTREC EMERGENCY No. 1-800-424-9300

NET CONTENTS:

LOT NO:

EXPIRATION DATE: